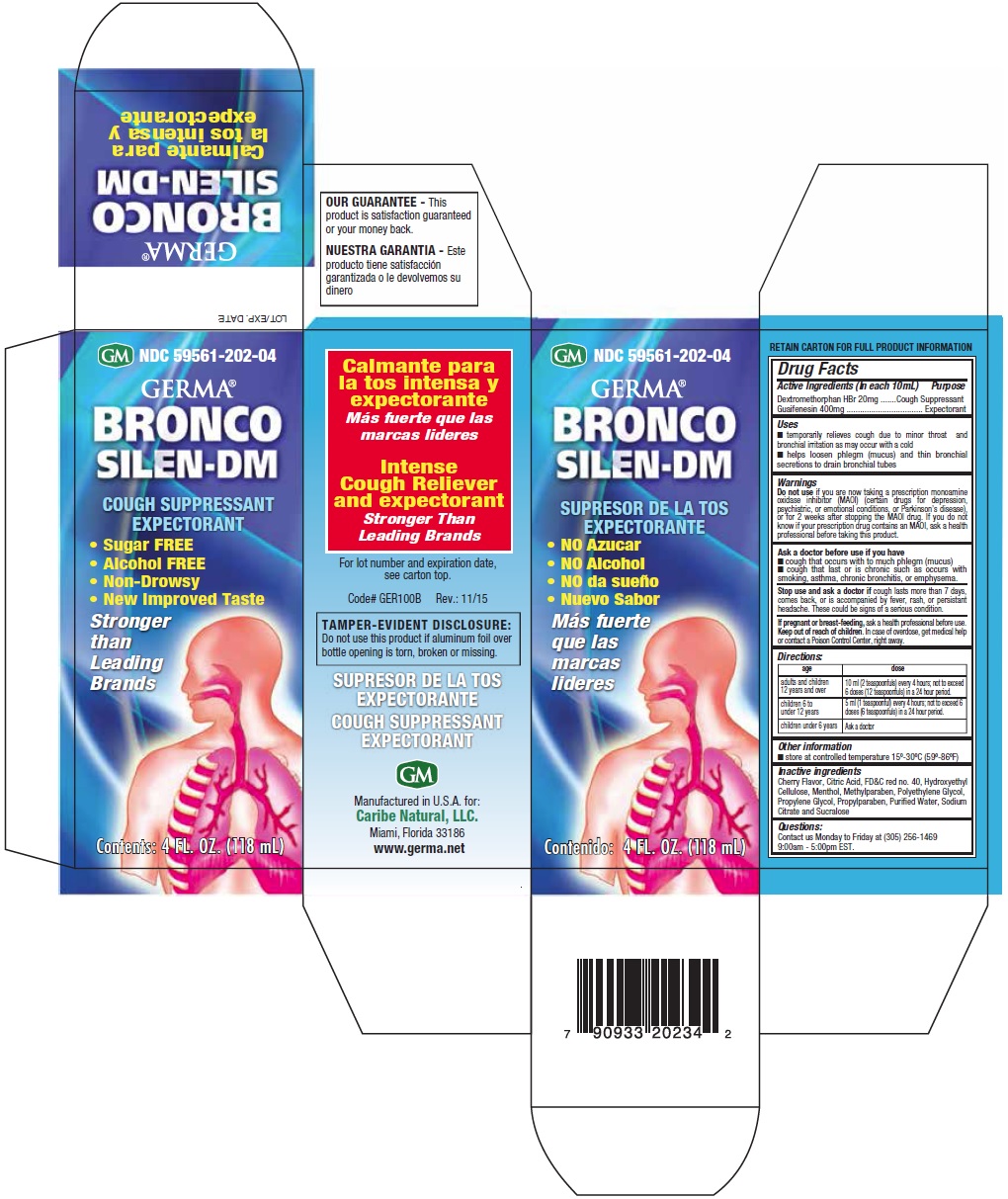 DRUG LABEL: BRONCO SILEN-DM
NDC: 59561-202 | Form: SOLUTION
Manufacturer: Caribe Natural, LLC
Category: otc | Type: HUMAN OTC DRUG LABEL
Date: 20151105

ACTIVE INGREDIENTS: DEXTROMETHORPHAN HYDROBROMIDE 20 mg/10 mL; GUAIFENESIN 400 mg/10 mL
INACTIVE INGREDIENTS: CITRIC ACID MONOHYDRATE; FD&C RED NO. 40; HYDROXYETHYL CELLULOSE (6500 MPA.S AT 2%); MENTHOL, UNSPECIFIED FORM; METHYLPARABEN; POLYETHYLENE GLYCOLS; PROPYLENE GLYCOL; PROPYLPARABEN; WATER; SODIUM CITRATE; SUCRALOSE

BRONCO SILEN-DM

Active Ingredients (in each 10mL)

Dextromethorphan HBr 20 mg
Guaifenesin 400 mg

Purpose

Cough Suppressant

Expectorant

Uses

- temporarily relieves cough due to minor throat and bronchial irritation may occur with a cold
- helps loosen phlegm (mucus) and thin bronchial secretions to drain bronchial tubes

Warnings

Do not use if you are now taking a prescription monoamine oxidase inhibitor (MAOI) (certain drugs for depression, psychiatric, or emotional conditions, or Parkinson’s disease), or for 2 weeks after stopping the MAOI drug. If you do not know if your prescription drug contains an MAOI, ask a health professional before taking this product.

Ask a doctor before use if you have

- cough that occurs with to much phlegm (mucus)
- cough that last or is chronic such as occurs with smoking, asthma, chronic bronchitis, or emphysema

Stop use and ask a doctor if cough lasts more than 7 days, comes back, or is accompanied by fever, rash, or persistent headache. These could be signs of a serious condition.

PREGNANCY OR BREAST FEEDING

If pregnant or breast-feeding, ask a health professional before use.

Keep out of reach of children. In case of accidental overdose, get medical help or contact a Poison Control Center right away.

Directions:

age | dose
adults and children 12 years and over | 10 ml (2 teaspoonfuls) every 4 hours; not to exceed 6 doses (12 teaspoonfuls) in a 24 hour period.
children 6 to under 12 years | 5 ml (1 teaspoonful) every 4 hours; not to exceed 6 doses (6 teaspoonfuls) in a 24 hour period.
children under 6 years | Ask a doctor

Other Information

- Store at room temperature 15° - 30ºC (59º - 86ºF)

Inactive ingredients

Cherry Flavor, Citric Acid, FD&C red no. 40, Hydroxyethyl Cellulose, Menthol, Methylparaben, Polyethylene Glycol, Propylene Glycol, Propylparaben, Purified Water, Sodium Citrate and Sucralose

Questions:

Contact us Monday to Friday at (305) 256-1469 9:00am - 5:00pm EST.

Display Label

NDC 59561-202-04
GERMA
BRONCO-SILEN-DM
COUGH SUPPRESSANT
EXPECTORANT
Sugar FREE
Alcohol FREE
Non-Drowsy
New Improved Taste
Stronger than Leading Brands
Contents: 4 FL. OZ. (118 mL)